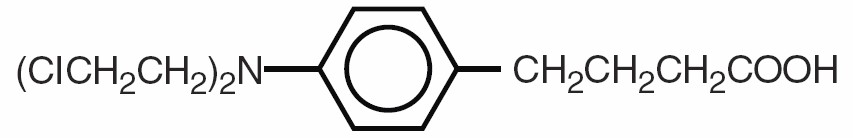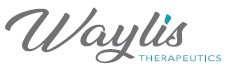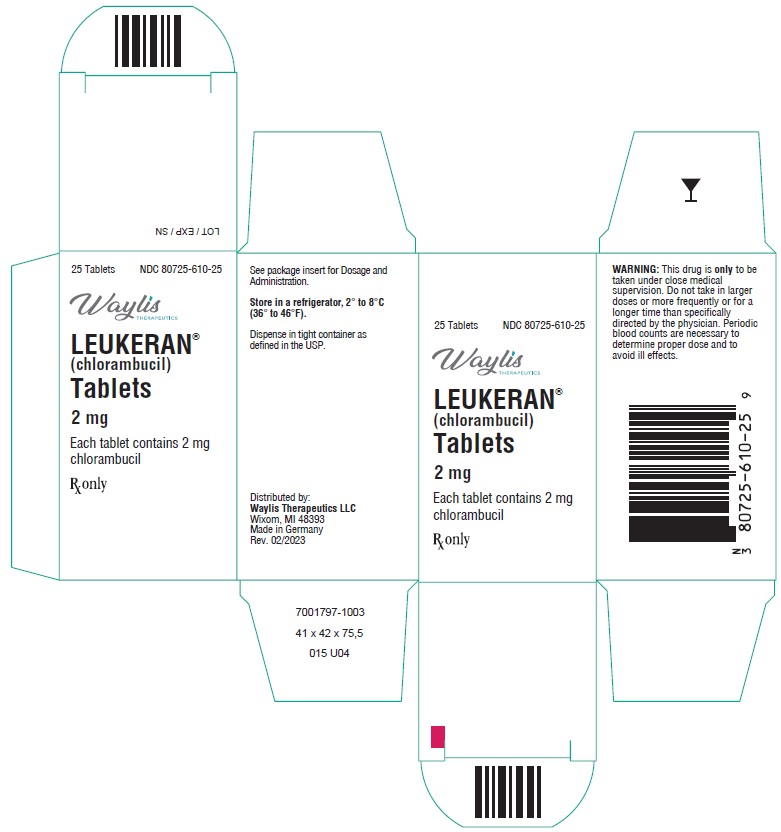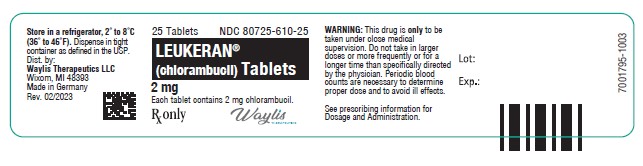 DRUG LABEL: LEUKERAN
NDC: 80725-610 | Form: TABLET, FILM COATED
Manufacturer: Waylis Therapeutics LLC
Category: prescription | Type: HUMAN PRESCRIPTION DRUG LABEL
Date: 20250108

ACTIVE INGREDIENTS: CHLORAMBUCIL 2 mg/1 1
INACTIVE INGREDIENTS: SILICON DIOXIDE; HYPROMELLOSES; ANHYDROUS LACTOSE; POLYETHYLENE GLYCOL, UNSPECIFIED; CELLULOSE, MICROCRYSTALLINE; FERRIC OXIDE RED; STEARIC ACID; TITANIUM DIOXIDE; FERRIC OXIDE YELLOW

LEUKERAN®
(chlorambucil) Tablets

WARNING

LEUKERAN (chlorambucil) can severely suppress bone marrow function. Chlorambucil is a carcinogen in humans. Chlorambucil is probably mutagenic and teratogenic in humans. Chlorambucil produces human infertility (see WARNINGS and PRECAUTIONS).

DESCRIPTION

LEUKERAN (chlorambucil) was first synthesized by Everett et al. It is a bifunctional alkylating agent of the nitrogen mustard type that has been found active against selected human neoplastic diseases.
Chlorambucil is known chemically as 4-[bis(2-chlorethyl)amino]benzenebutanoic acid and has the following structural formula:

Chlorambucil hydrolyzes in water and has a pKa of 5.8.
LEUKERAN (chlorambucil) is available in tablet form for oral administration. Each film-coated tablet contains 2 mg chlorambucil and the inactive ingredients colloidal silicon dioxide, hypromellose, lactose (anhydrous), macrogol/PEG 400, microcrystalline cellulose, red iron oxide, stearic acid, titanium dioxide, and yellow iron oxide.

CLINICAL PHARMACOLOGY

Mechanism of Action

Chlorambucil, an aromatic nitrogen mustard derivative, is an alkylating agent. Chlorambucil interferes with DNA replication and induces cellular apoptosis via the accumulation of cytosolic p53 and subsequent activation of Bax, an apoptosis promoter.

PHARMACOKINETICS

In a study of 12 patients given single oral doses of 0.2 mg/kg of LEUKERAN, the mean dose-adjusted (±SD) plasma chlorambucil Cmax was 492 ± 160 ng/mL, the AUC was 883 ± 329 ng.h/mL, the mean elimination half-life (t½) was 1.3 ± 0.5 hours, and the Tmax was 0.83 ± 0.53 hours. For the major metabolite, phenylacetic acid mustard (PAAM), the mean dose-adjusted (± SD) plasma Cmax was 306 ± 73 ng/mL, the AUC was 1204 ± 285 ng.h/mL, mean t½ was 1.8 ± 0.4 hours, and the Tmax was 1.9 ± 0.7 hours.
After single oral doses of 0.6 to 1.2 mg/kg, peak plasma chlorambucil levels (Cmax) are reached within 1 hour and the terminal elimination half-life (t½) of the parent drug is estimated at 1.5 hours.
Absorption: Chlorambucil is rapidly and completely (>70%) absorbed from the gastrointestinal tract. Consistent with the rapid, predictable absorption of chlorambucil, the inter-individual variability in the plasma pharmacokinetics of chlorambucil has been shown to be relatively small following oral dosages of between 15 and 70 mg (2-fold intra-patient variability, and a 2 to 4 fold interpatient variability in AUC). The absorption of chlorambucil is reduced when taken after food. In a study of ten patients, food intake increased the median Tmax by 2-fold and reduced the dose-adjusted Cmax and AUC values by 55% and 20%, respectively.
Distribution: The apparent volume of distribution averaged 0.31 L/kg following a single 0.2 mg/kg oral dose of chlorambucil in 11 cancer patients with chronic lymphocytic leukemia. Chlorambucil and its metabolites are extensively bound to plasma and tissue proteins. In vitro, chlorambucil is 99% bound to plasma proteins, specifically albumin. Cerebrospinal fluid levels of chlorambucil have not been determined.
Metabolism: Chlorambucil is extensively metabolized in the liver primarily to phenylacetic acid mustard, which has antineoplastic activity. Chlorambucil and its major metabolite undergo oxidative degradation to monohydroxy and dihydroxy derivatives.
Excretion: After a single dose of radiolabeled chlorambucil (^14C), approximately 20% to 60% of the radioactivity appears in the urine after 24 hours. Again, less than 1% of the urinary radioactivity is in the form of chlorambucil or phenylacetic acid mustard.

INDICATIONS AND USAGE

LEUKERAN (chlorambucil) is indicated in the treatment of chronic lymphatic (lymphocytic) leukemia, malignant lymphomas including lymphosarcoma, giant follicular lymphoma, and Hodgkin’s disease. It is not curative in any of these disorders but may produce clinically useful palliation.

CONTRAINDICATIONS

Chlorambucil should not be used in patients whose disease has demonstrated a prior resistance to the agent. Patients who have demonstrated hypersensitivity to chlorambucil should not be given the drug.
There may be cross-hypersensitivity (skin rash) between chlorambucil and other alkylating agents.

WARNINGS

Because of its carcinogenic properties, chlorambucil should not be given to patients with conditions other than chronic lymphatic leukemia or malignant lymphomas. Convulsions, infertility, leukemia, and secondary malignancies have been observed when chlorambucil was employed in the therapy of malignant and non-malignant diseases.
There are many reports of acute leukemia arising in patients with both malignant and non-malignant diseases following chlorambucil treatment. In many instances, these patients also received other chemotherapeutic agents or some form of radiation therapy. The quantitation of the risk of chlorambucil-induction of leukemia or carcinoma in humans is not possible. Evaluation of published reports of leukemia developing in patients who have received chlorambucil (and other alkylating agents) suggests that the risk of leukemogenesis increases with both chronicity of treatment and large cumulative doses. However, it has proved impossible to define a cumulative dose below which there is no risk of the induction of secondary malignancy. The potential benefits from chlorambucil therapy must be weighed on an individual basis against the possible risk of the induction of a secondary malignancy.
Chlorambucil has been shown to cause chromatid or chromosome damage in humans. Both reversible and permanent sterility have been observed in both sexes receiving chlorambucil.
A high incidence of sterility has been documented when chlorambucil is administered to prepubertal and pubertal males. Prolonged or permanent azoospermia has also been observed in adult males. While most reports of gonadal dysfunction secondary to chlorambucil have related to males, the induction of amenorrhea in females with alkylating agents is well documented and chlorambucil is capable of producing amenorrhea. Autopsy studies of the ovaries from women with malignant lymphoma treated with combination chemotherapy including chlorambucil have shown varying degrees of fibrosis, vasculitis, and depletion of primordial follicles.
Rare instances of skin rash progressing to erythema multiforme, toxic epidermal necrolysis, or Stevens-Johnson syndrome have been reported. Chlorambucil should be discontinued promptly in patients who develop skin reactions.

Pregnancy

Chlorambucil can cause fetal harm when administered to a pregnant woman. Unilateral renal agenesis has been observed in 2 offspring whose mothers received chlorambucil during the first trimester. Urogenital malformations, including absence of a kidney, were found in fetuses of rats given chlorambucil. There are no adequate and well-controlled studies in pregnant women. If this drug is used during pregnancy, or if the patient becomes pregnant while taking this drug, the patient should be apprised of the potential hazard to the fetus. Women of childbearing potential should be advised to avoid becoming pregnant.

PRECAUTIONS

General

Many patients develop a slowly progressive lymphopenia during treatment. The lymphocyte count usually rapidly returns to normal levels upon completion of drug therapy. Most patients have some neutropenia after the third week of treatment and this may continue for up to 10 days after the last dose. Subsequently, the neutrophil count usually rapidly returns to normal. Severe neutropenia appears to be related to dosage and usually occurs only in patients who have received a total dosage of 6.5 mg/kg or more in one course of therapy with continuous dosing. About one quarter of all patients receiving the continuous-dose schedule, and one third of those receiving this dosage in 8 weeks or less may be expected to develop severe neutropenia.
While it is not necessary to discontinue chlorambucil at the first evidence of a fall in neutrophil count, it must be remembered that the fall may continue for 10 days after the last dose, and that as the total dose approaches 6.5 mg/kg, there is a risk of causing irreversible bone marrow damage. The dose of chlorambucil should be decreased if leukocyte or platelet counts fall below normal values and should be discontinued for more severe depression.
Chlorambucil should not be given at full dosages before 4 weeks after a full course of radiation therapy or chemotherapy because of the vulnerability of the bone marrow to damage under these conditions. If the pretherapy leukocyte or platelet counts are depressed from bone marrow disease process prior to institution of therapy, the treatment should be instituted at a reduced dosage.
Persistently low neutrophil and platelet counts or peripheral lymphocytosis suggest bone marrow infiltration. If confirmed by bone marrow examination, the daily dosage of chlorambucil should not exceed 0.1 mg/kg. Chlorambucil appears to be relatively free from gastrointestinal side effects or other evidence of toxicity apart from the bone marrow depressant action. In humans, single oral doses of 20 mg or more may produce nausea and vomiting.
Children with nephrotic syndrome and patients receiving high pulse doses of chlorambucil may have an increased risk of seizures. As with any potentially epileptogenic drug, caution should be exercised when administering chlorambucil to patients with a history of seizure disorder or head trauma, or who are receiving other potentially epileptogenic drugs.
Administration of live vaccines to immunocompromised patients should be avoided.

INFORMATION FOR PATIENTS

Patients should be informed that the major toxicities of chlorambucil are related to hypersensitivity, drug fever, myelosuppression, hepatotoxicity, infertility, seizures, gastrointestinal toxicity, and secondary malignancies. Patients should never be allowed to take the drug without medical supervision and should consult their physician if they experience skin rash, bleeding, fever, jaundice, persistent cough, seizures, nausea, vomiting, amenorrhea, or unusual lumps/masses. Women of childbearing potential should be advised to avoid becoming pregnant.

Laboratory Tests

Patients must be followed carefully to avoid life-endangering damage to the bone marrow during treatment. Weekly examination of the blood should be made to determine hemoglobin levels, total and differential leukocyte counts, and quantitative platelet counts. Also, during the first 3 to 6 weeks of therapy, it is recommended that white blood cell counts be made 3 or 4 days after each of the weekly complete blood counts. Galton et al have suggested that in following patients it is helpful to plot the blood counts on a chart at the same time that body weight, temperature, spleen size, etc., are recorded. It is considered dangerous to allow a patient to go more than 2 weeks without hematological and clinical examination during treatment.

Drug Interactions

There are no known drug/drug interactions with chlorambucil.

Carcinogenesis, Mutagenesis, Impairment of Fertility

See WARNINGS section for information on carcinogenesis, mutagenesis, and impairment of fertility.

Pregnancy

Teratogenic Effects: See WARNINGS section.

Lactation

It is not known whether this drug is excreted in human milk. Because many drugs are excreted in human milk and because of the potential for serious adverse reactions in nursing infants from chlorambucil, a decision should be made whether to discontinue nursing or to discontinue the drug, taking into account the importance of the drug to the mother.

Pediatric Use

The safety and effectiveness in pediatric patients have not been established.

Geriatric Use

Clinical studies of chlorambucil did not include sufficient numbers of subjects aged 65 and over to determine whether they respond differently from younger subjects. Other reported clinical experience has not identified differences in responses between the elderly and younger patients. In general, dose selection for an elderly patient should be cautious, usually starting at the low end of the dosing range, reflecting the greater frequency of decreased hepatic, renal, or cardiac function, and of concomitant disease or other drug therapy.
Use in Patients with Renal Impairment: The impact of renal impairment on chlorambucil elimination has not been formally studied. The renal elimination of unchanged chlorambucil and its major active metabolites, phenylacetic acid mustard, represents less than 1% of the administered dose. In addition, no dose adjustment was required in 2 dialysis patients on chlorambucil. Therefore, renal impairment is not expected to significantly impact the elimination of chlorambucil.
Use in Patients with Hepatic Impairment: No formal studies have been conducted in patients with hepatic impairment. As chlorambucil is primarily metabolized in the liver, patients with hepatic impairment should be closely monitored for toxicity and dose reduction may be considered in patients with hepatic impairment when treated with LEUKERAN (see DOSAGE AND ADMINISTRATION).

ADVERSE REACTIONS

To report SUSPECTED ADVERSE REACTIONS, contact Waylis Therapeutics LLC Toll-Free at 1-888-514-4727 or FDA at 1-800-FDA-1088 or www.fda.gov/medwatch.

Hematologic

The most common side effect is bone marrow suppression, anemia, leukopenia, neutropenia, thrombocytopenia, or pancytopenia. Although bone marrow suppression frequently occurs, it is usually reversible if the chlorambucil is withdrawn early enough. However, irreversible bone marrow failure has been reported.

Gastrointestinal

Gastrointestinal disturbances such as nausea and vomiting, diarrhea, and oral ulceration occur infrequently.

CNS

Tremors, muscular twitching, myoclonia, confusion, agitation, ataxia, flaccid paresis, and hallucinations have been reported as rare adverse experiences to chlorambucil which resolve upon discontinuation of drug. Rare, focal and/or generalized seizures have been reported to occur in both children and adults at both therapeutic daily doses and pulse-dosing regimens, and in acute overdose (see PRECAUTIONS: General).

Dermatologic

Allergic reactions such as urticaria and angioneurotic edema have been reported following initial or subsequent dosing. Skin hypersensitivity (including rare reports of skin rash progressing to erythema multiforme, toxic epidermal necrolysis, and Stevens-Johnson syndrome) has been reported (see WARNINGS).

Miscellaneous

Other reported adverse reactions include: pulmonary fibrosis, hepatotoxicity and jaundice, drug fever, peripheral neuropathy, interstitial pneumonia, sterile cystitis, infertility, leukemia, and secondary malignancies (see WARNINGS).

OVERDOSAGE

Reversible pancytopenia was the main finding of inadvertent overdoses of chlorambucil.

Neurological toxicity ranging from agitated behavior and ataxia to multiple grand mal seizures has also occurred. As there is no known antidote, the blood picture should be closely monitored and general supportive measures should be instituted, together with appropriate blood transfusions, if necessary. Chlorambucil is not dialyzable.
Oral LD50 single doses in mice are 123 mg/kg. In rats, a single intraperitoneal dose of 12.5 mg/kg of chlorambucil produces typical nitrogen-mustard effects; these include atrophy of the intestinal mucous membrane and lymphoid tissues, severe lymphopenia becoming maximal in 4 days, anemia, and thrombocytopenia. After this dose, the animals begin to recover within 3 days and appear normal in about a week, although the bone marrow may not become completely normal for about 3 weeks. An intraperitoneal dose of 18.5 mg/kg kills about 50% of the rats with development of convulsions. As much as 50 mg/kg has been given orally to rats as a single dose, with recovery. Such a dose causes bradycardia, excessive salivation, hematuria, convulsions, and respiratory dysfunction.

DOSAGE AND ADMINISTRATION

The usual oral dosage is 0.1 to 0.2 mg/kg body weight daily for 3 to 6 weeks as required. This usually amounts to 4 to 10 mg per day for the average patient. The entire daily dose may be given at one time. These dosages are for initiation of therapy or for short courses of treatment. The dosage must be carefully adjusted according to the response of the patient and must be reduced as soon as there is an abrupt fall in the white blood cell count. Patients with Hodgkin’s disease usually require 0.2 mg/kg daily, whereas patients with other lymphomas or chronic lymphocytic leukemia usually require only 0.1 mg/kg daily. When lymphocytic infiltration of the bone marrow is present, or when the bone marrow is hypoplastic, the daily dose should not exceed 0.1 mg/kg (about 6 mg for the average patient). Alternate schedules for the treatment of chronic lymphocytic leukemia employing intermittent, biweekly, or once-monthly pulse doses of chlorambucil have been reported. Intermittent schedules of chlorambucil begin with an initial single dose of 0.4 mg/kg. Doses are generally increased by 0.1 mg/kg until control of lymphocytosis or toxicity is observed. Subsequent doses are modified to produce mild hematologic toxicity. It is felt that the response rate of chronic lymphocytic leukemia to the biweekly or once-monthly schedule of chlorambucil administration is similar or better to that previously reported with daily administration and that hematologic toxicity was less than or equal to that encountered in studies using daily chlorambucil.
Radiation and cytotoxic drugs render the bone marrow more vulnerable to damage, and chlorambucil should be used with particular caution within 4 weeks of a full course of radiation therapy or chemotherapy. However, small doses of palliative radiation over isolated foci remote from the bone marrow will not usually depress the neutrophil and platelet count. In these cases chlorambucil may be given in the customary dosage.
It is presently felt that short courses of treatment are safer than continuous maintenance therapy, although both methods have been effective. It must be recognized that continuous therapy may give the appearance of “maintenance” in patients who are actually in remission and have no immediate need for further drug. If maintenance dosage is used, it should not exceed 0.1 mg/kg daily and may well be as low as 0.03 mg/kg daily. A typical maintenance dose is 2 mg to 4 mg daily, or less, depending on the status of the blood counts. It may, therefore, be desirable to withdraw the drug after maximal control has been achieved, since intermittent therapy reinstituted at time of relapse may be as effective as continuous treatment.

Procedures for proper handling and disposal of anticancer drugs should be used. Several guidelines on this subject have been published.^1-4 There is no general agreement that all of the procedures recommended in the guidelines are necessary or appropriate.

SPECIAL POPULATIONS

Hepatic Impairment: Patients with hepatic impairment should be closely monitored for toxicity. As chlorambucil is primarily metabolized in the liver, dose reduction may be considered in patients with hepatic impairment when treated with LEUKERAN. However, there are insufficient data in patients with hepatic impairment to provide a specific dosing recommendation.

HOW SUPPLIED

LEUKERAN is supplied as brown, film-coated, round, biconvex tablets containing 2 mg chlorambucil in amber glass bottles with child-resistant closures. One side is engraved with “GX EG3” and the other side is engraved with an “L.”
Bottle of 25 (NDC 80725-610-25)

Store in a refrigerator, 2° to 8°C (36° to 46°F).

REFERENCES

1. NIOSH Alert: Preventing occupational exposures to antineoplastic and other hazardous drugs in healthcare settings. 2004. U.S. Department of Health and Human Services, Public Health Service, Centers for Disease Control and Prevention, National Institute for Occupational Safety and Health, DHHS (NIOSH) Publication No. 2004-165.

2. OSHA Technical Manual, TED 1-0.15A, Section VI: Chapter 2. Controlling Occupational Exposure to Hazardous Drugs. OSHA, 1999. http://www.osha.gov/dts/osta/otm/otm_vi/otm_vi_2.html

3. American Society of Health-System Pharmacists. ASHP guidelines on handling hazardous drugs. Am J Health-Syst Pharm. (2006) 63:1172-1193.

4. Polovich, M., White, J. M., & Kelleher, L.O. (eds.) 2005. Chemotherapy and biotherapy guidelines and recommendations for practice (2nd. ed.) Pittsburgh, PA: Oncology Nursing Society.

Distributed by: Waylis Therapeutics LLC
Wixom, MI 48393
Made in Germany
Rev. 02/2023

PACKAGE LABEL PRINCIPAL DISPLAY PANEL

Principal Display Panel

NDC 80725-610-25

LEUKERAN®

(chlorambucil) Tablets

2 mg

25 Tablets

Each tablet contains 2 mg chlorambucil.

Rx Only.

Leukeran 2mg 25 ct. Carton

Leukeran 2mg 25 ct. Label